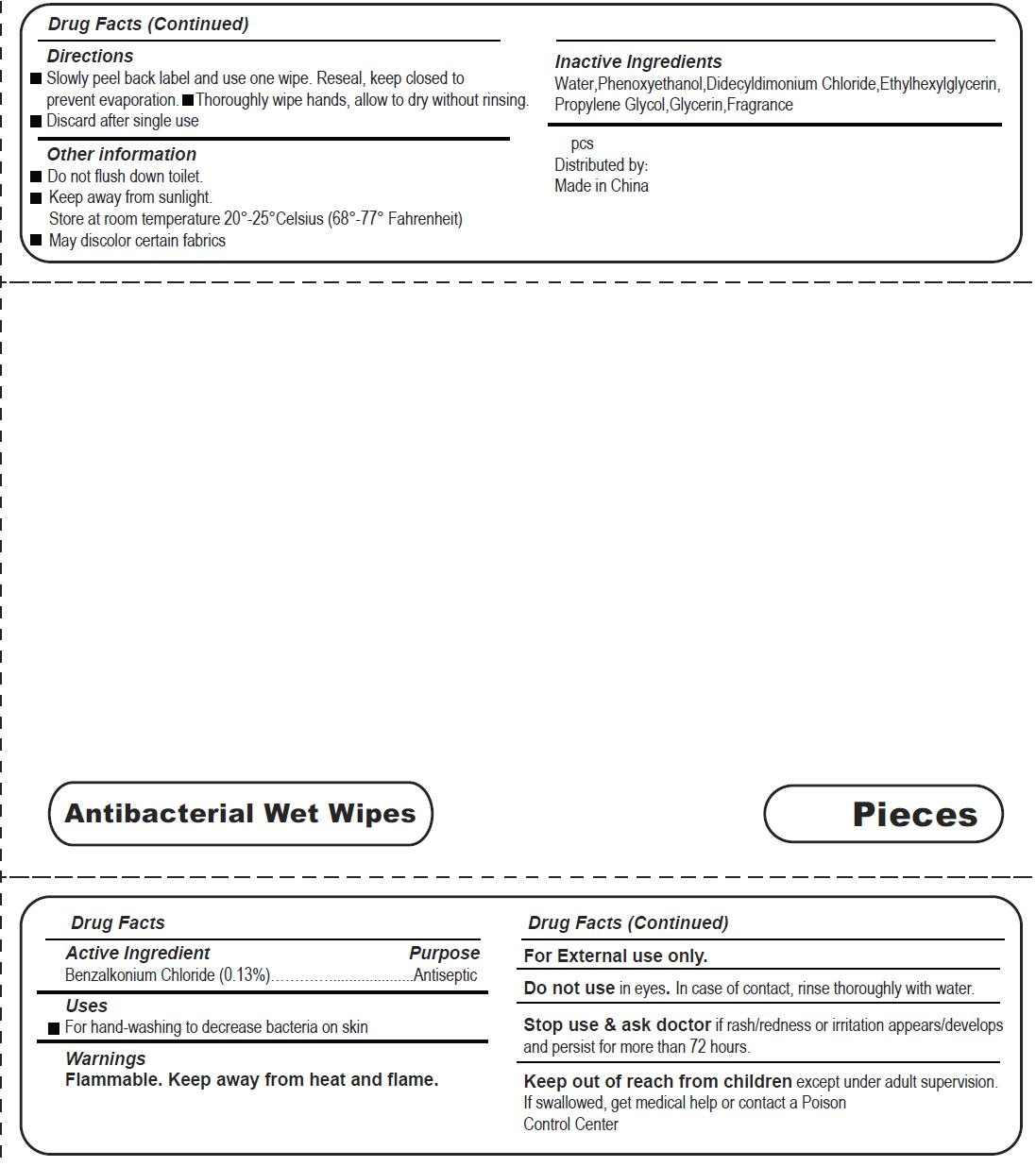 DRUG LABEL: Antibacterial Wet Wipes
NDC: 79293-001 | Form: CLOTH
Manufacturer: Hangzhou Fangyuan Textile Co., Ltd.
Category: otc | Type: HUMAN OTC DRUG LABEL
Date: 20220114

ACTIVE INGREDIENTS: BENZALKONIUM CHLORIDE 0.13 g/100 g
INACTIVE INGREDIENTS: ETHYLHEXYLGLYCERIN; WATER; PROPYLENE GLYCOL; PHENOXYETHANOL; DIDECYLDIMONIUM CHLORIDE; GLYCERIN

79293-001 Antibacterial Wet Wipes 0.13% Benzalkonium Chloride

Active Ingredient

Benzalkonium Chloride 0.13%

Purpose

Antiseptic

USE

■For hand-washing to decrease bacteria on skin

Warning

For External use only.
DO not use in eyes. In case of contact, rinse thoroughly with water.
Stop use & ask doctor if rash/redness or irritation appears/develops
and persist for more than 72 hours.
Flammable. Keep away from heat and flame.

KEEP OUT OF REACH OF CHILDREN

Keep out of reach from children except under adult supervision.
If swallowed, get medical help or contact a Poison
Control Center

Directions

Slowly peel back label and use one wipe. Reseal, keep closed to prevent evaporation. Thoroughly wipe hands, allow to dry without rinsing.
Discard after single use

Inactive ingredients

Water, Phenoxyethanol,Didecyldimonium Chloride ,Ethyhexylglycerin, Propylene Glycol, Glycerin, Fragrance